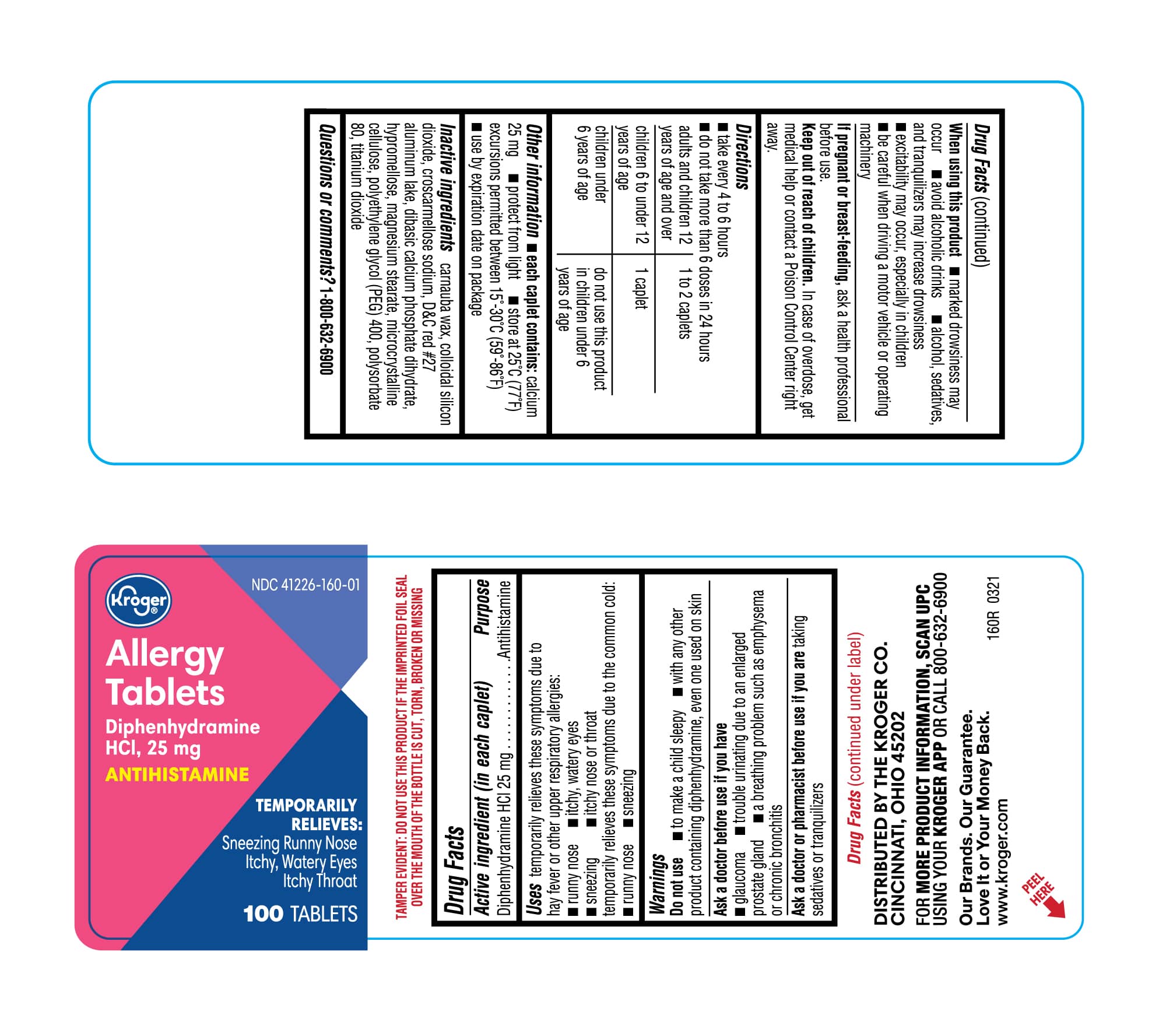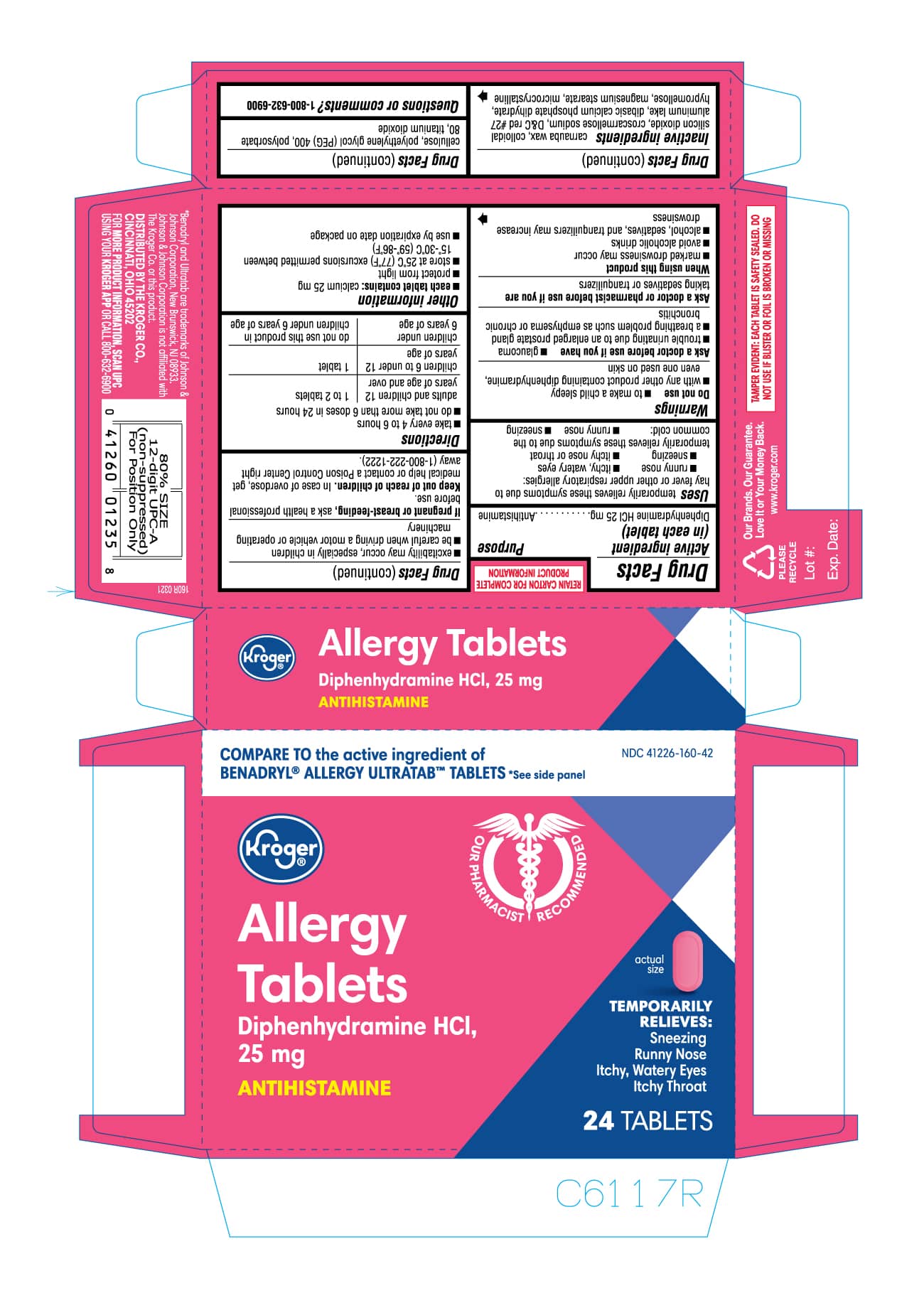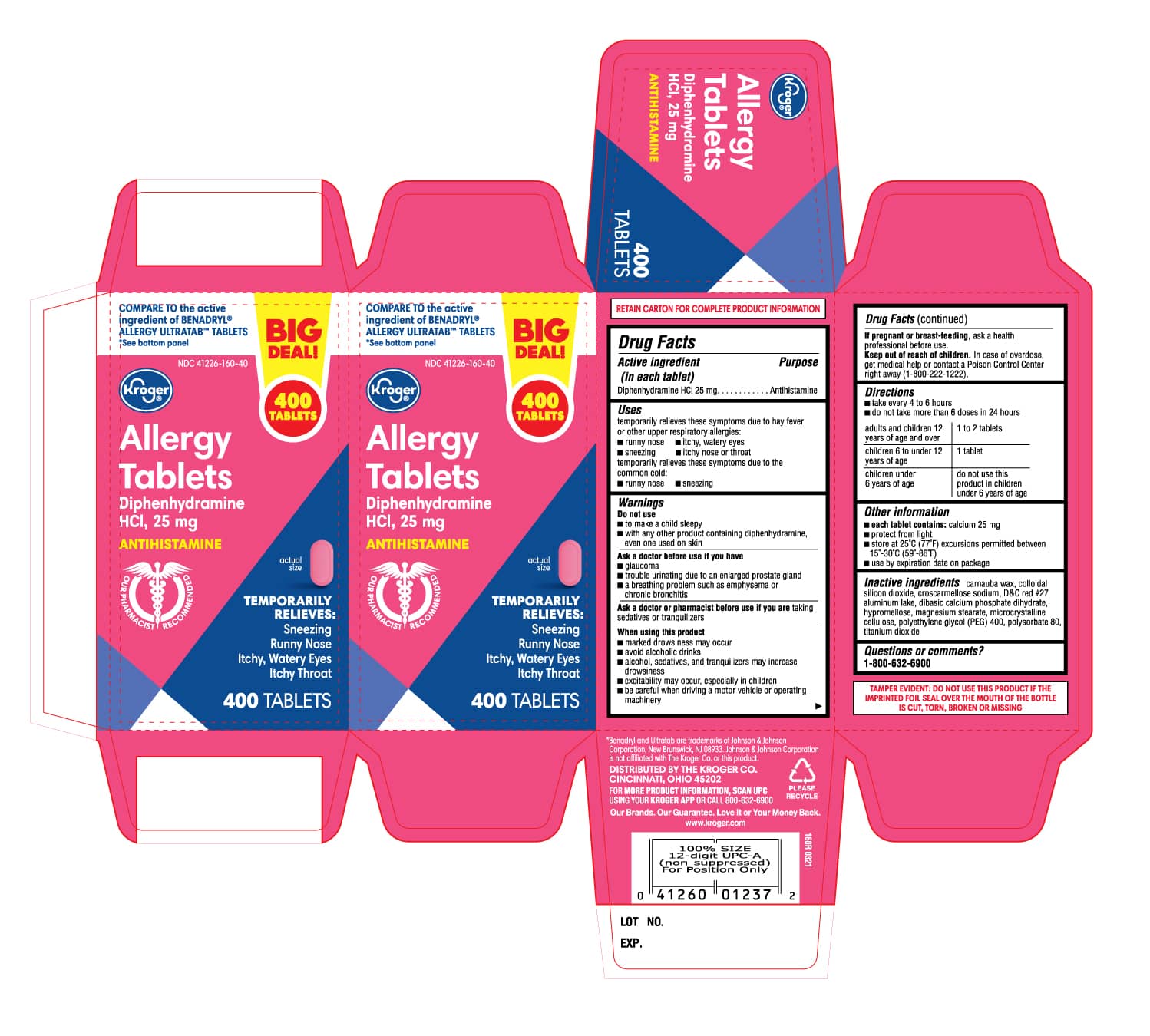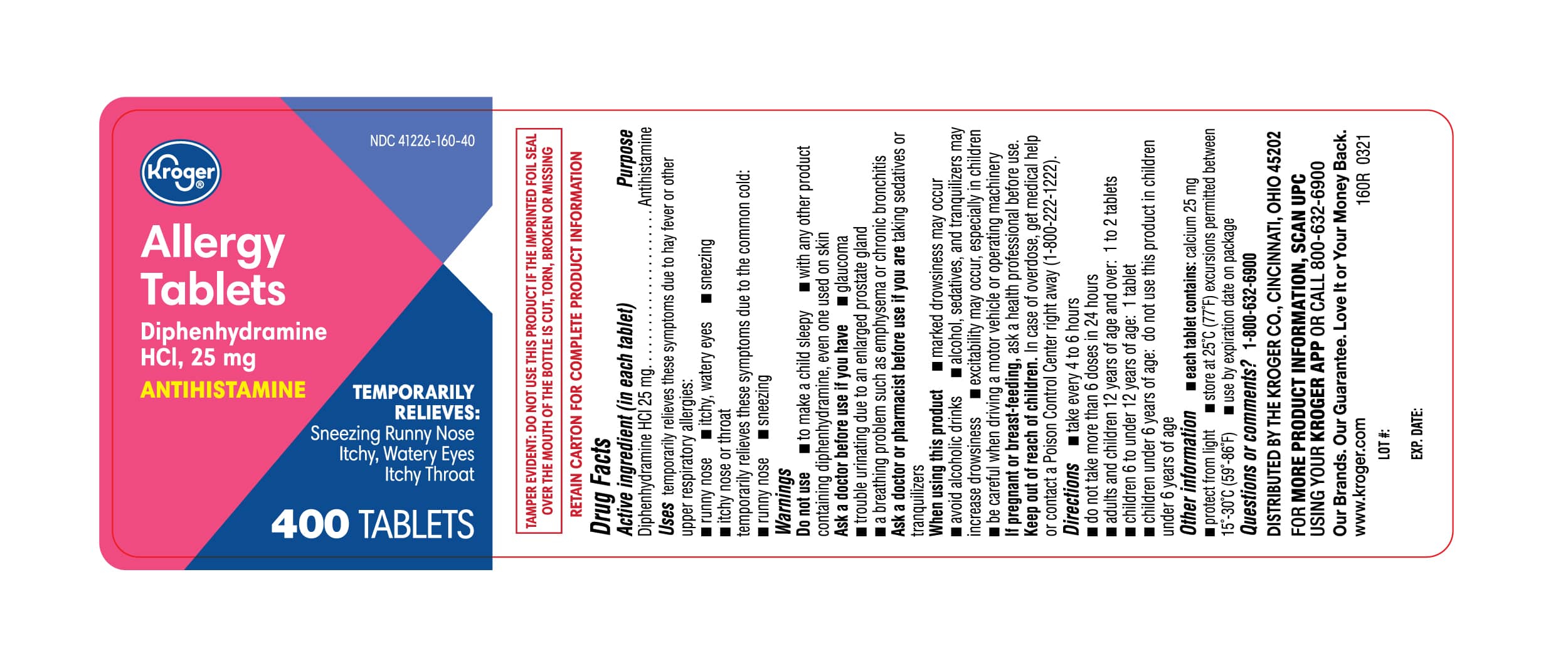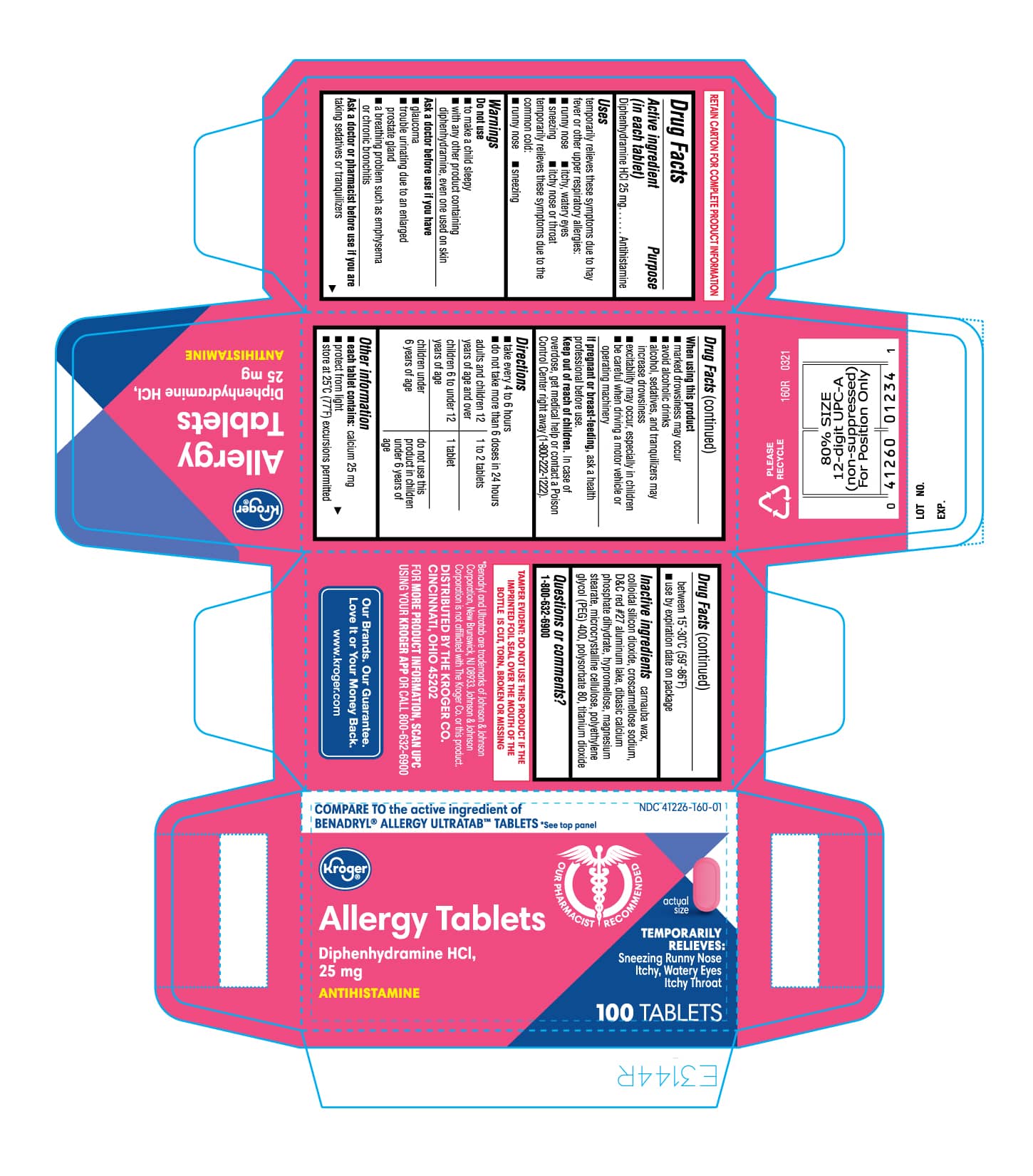 DRUG LABEL: ALLERGY
NDC: 41226-160 | Form: TABLET, FILM COATED
Manufacturer: Kroger Company
Category: otc | Type: HUMAN OTC DRUG LABEL
Date: 20250625

ACTIVE INGREDIENTS: DIPHENHYDRAMINE HYDROCHLORIDE 25 mg/1 1
INACTIVE INGREDIENTS: DIBASIC CALCIUM PHOSPHATE DIHYDRATE; POLYSORBATE 80; TITANIUM DIOXIDE; HYPROMELLOSES; POLYETHYLENE GLYCOL 400; MAGNESIUM STEARATE; CROSCARMELLOSE SODIUM; CARNAUBA WAX; SILICON DIOXIDE; D&C RED NO. 27 ALUMINUM LAKE; MICROCRYSTALLINE CELLULOSE

160R KROGER 41226 160 Diphenhydramine Hydrochloride Tablets

Active ingredient (in each tablet)

Diphenhydramine HCl 25 mg

Purpose

Antihistamine

Uses
temporarily relieves these symptoms due to hay fever or other upper respiratory allergies:

- runny nose
- itchy, watery eyes
- sneezing
- itchy nose or throat

temporarily relieves these symptoms due to the common cold:

- runny nose
- sneezing

Warnings

Do not use

- to make a child sleepy
- with any other product containing diphenhydramine, even one used on skin

Ask a doctor before use if you have

- glaucoma
- trouble urinating due to an enlarged prostate gland
- a breathing problem such as emphysema or chronic bronchitis

Ask a doctor or pharmacist before use if you are taking sedatives or tranquilizers

When using this product

- marked drowsiness may occur
- avoid alcoholic drinks
- alcohol, sedatives, and tranquilizers may increase drowsiness
- excitability may occur, especially in children
- be careful when driving a motor vehicle or operating machinery

PREGNANCY OR BREAST FEEDING

If pregnant or breast-feeding, ask a health professional before use.

Keep out of reach of children. In case of overdose, get medical help or contact a Poison Control Center right away (1-800-222-1222).

Directions

- take every 4 to 6 hours
- do not take more than 6 doses in 24 hours

adults and children 12 years and over | 1 to 2 tablets
children 6 to under 12 years | 1 to 2 tablets
children under 6 years | 1 to 2 tablets

Other information

- each caplet contains: calcium 25 mg
- protect from light
- store at 25°C (77°F) excursions permitted 15°-30°C (59°-86°F)
- use by expiration date on package

INACTIVE INGREDIENT

Inactive ingredients carnauba wax, colloidal silicon dioxide, croscarmellose sodium, D&C red #27 aluminum lake, dibasic calcium phosphate dihydrate, hypromellose, magnesium stearate, microcrystalline cellulose, polyethylene glycol (PEG) 400, polysorbate 80, titanium dioxidede

Questions or comments? Call 1-800-632-6900

PACKAGE LABEL

Allergy 400ct Carton

Allergy 400ct Label

Allergy 100ct Carton

Allergy 100ct label

Allergy 24ct Carton